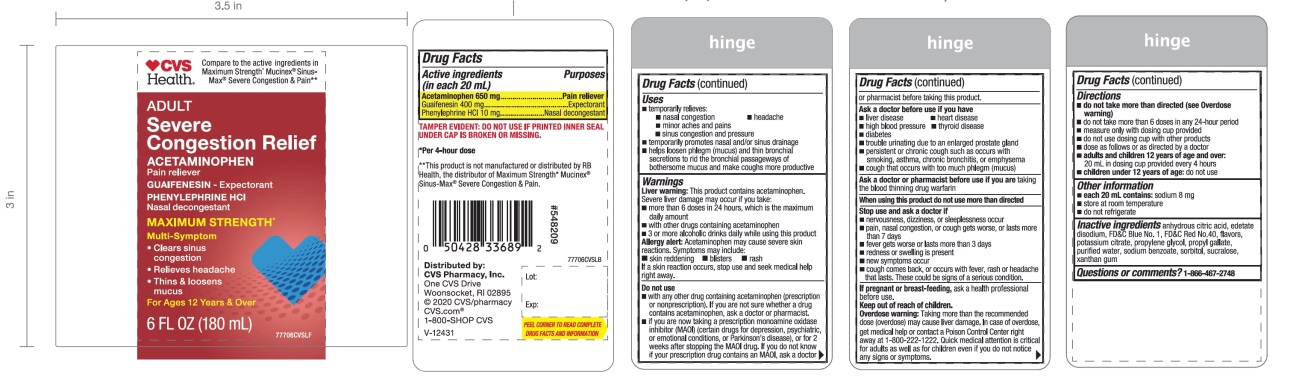 DRUG LABEL: CVS Severe Congestion and Pain Relief
NDC: 69842-717 | Form: SOLUTION
Manufacturer: CVS
Category: otc | Type: HUMAN OTC DRUG LABEL
Date: 20251210

ACTIVE INGREDIENTS: ACETAMINOPHEN 650 mg/20 mL; GUAIFENESIN 400 mg/20 mL; PHENYLEPHRINE HYDROCHLORIDE 10 mg/20 mL
INACTIVE INGREDIENTS: ANHYDROUS CITRIC ACID; EDETATE DISODIUM; FD&C BLUE NO. 1; FD&C RED NO. 40; POTASSIUM CITRATE; PROPYLENE GLYCOL; PROPYL GALLATE; WATER; SODIUM BENZOATE; SORBITOL; SUCRALOSE; XANTHAN GUM

CVS Severe Congestion Maximum Strength

Drug Facts

ACTIVE INGREDIENT

PURPOSE

Active ingredients (in each 20 mL) | Purposes
Acetaminophen 650 mg | Pain reliever
Guaifenesin 400 mg | Expectorant
Phenylephrine HCl 10 mg | Nasal decongestant

Uses

- temporarily relieves:
  - nasal congestion
  - headache
  - minor aches and pains
  - sinus congestion and pressure
- temporarily promotes nasal and/or sinus drainage
- helps loosens phlegm (mucus) and thin bronchial secretions to rid the bronchial passageways of bothersome mucus and make coughs more productive

Warnings

Liver warning

This product contains acetaminophen. Severe liver damage may occur if you take:

- more than 6 doses in 24 hours, which is the maximum daily amount
- with other drugs containing acetaminophen
- 3 or more alcoholic drinks daily while using this product

Allergy alert

Acetaminophen may cause severe skin reactions. Symptoms may include:

- skin reddening
- blisters
- rash

If a skin reaction occurs, stop use and seek medical help right away.

Do not use

- with any other drug containing acetaminophen (prescription or nonprescription). If you are not sure whether a drug contains acetaminophen, ask a doctor or pharmacist.
- if you are now taking a prescription monoamine oxidase inhibitor (MAOI) (certain drugs for depression, psychiatric, or emotional conditions, or Parkinson's disease), or for 2 weeks after stopping the MAOI drug. If you do not know if your prescription drug contains an MAOI, ask a doctor or pharmacist before taking this product.

Ask a doctor before use if you have

- liver disease
- heart disease
- high blood pressure
- thyroid disease
- diabetes
- trouble urinating due to an enlarged prostate gland
- persistent or chronic cough such as occurs with smoking, asthma, chronic bronchitis, or emphysema
- cough that occurs with too much phlegm (mucus)

Ask a doctor or pharmacist before use if you aretaking the blood thinning drug warfarin

Stop use and ask a doctor if

- nervousness, dizziness, or sleeplessness occur
- pain, nasal congestion, or cough gets worse or lasts more than 7 days
- fever gets worse or lasts more than 3 days
- redness or swelling is present
- new symptoms occur
- cough comes back, or occurs with rash or headache that lasts. These could be signs of a serious condition.

PREGNANCY OR BREAST FEEDING

If pregnant or breast-feeding,ask a health professional before use.

Keep out of reach of children.

Overdose warning

Taking more than the recommended dose (overdose) may cause liver damage. In case of overdose, get medical help or contact a Poison Control Center right away at 1-800-222-1222. Quick medical attention is critical for adults as well as for children even if you do not notice any signs or symptoms.

Directions

- do not take more than directed (see Overdose warning)
- do not take more than 6 doses in any 24-hour period
- measure only with dosing cup provided
- do not use dosing cup with other products
- dose as follows or as directed by a doctor
- adults and children 12 years of age and older: 20 mL in dosing cup provided every 4 hours
- children under 12 years of age:do not use

Other information

- each 20 mL contains:sodium 8 mg
- store at room temperature
- do not refrigerate

Inactive ingredients

anhydrous citric acid, edetate disodium, FD&C Blue no. 1, FD&C Red no. 40, flavors, potassium citrate, propylene glycol, propyl gallate, purified water, sodium benzoate, sorbitol, sucralose, xanthan gum

Questions or comments?

1-866-467-2748

PRINCIPAL DISPLAY PANEL - 180 mL Bottle Label

Compare to the active ingredients Maximum Strength* Mucinex® Sinus-Max®Severe Congestion & Pain**

NDC 63824-261-66

ADULT

Severe Congestion Pain Reliever

Acetaminophen– Pain Reliever
GUAIFENESIN – Expectorant
PHENYLEPHRINE HCl – Nasal Decongestant

MAXIMUM STRENGTH*

Multi-Symptom

- Clears Sinus Congestion
- Relieves Headache
- Thins & Loosens Mucus

For Ages 12 Years & Over

6 FL OZ (180mL)

TAMPER EVIDENT: DO NOT USE IF PRINTED INNER SEAL UNDER CAP IS BROKEN OR MISSING.

*Per 4- hour dose

Distributed by:

CVS Pharmacy, Inc.

One CVS Drive

Woonsocket, RI 02985

© 2020 CVS/pharmacy

CVS.com

1-800-SHOP CVS

V-12431

*This product is not manufactured or distributed by RB Health, the distributor of Maximum Strength* Mucinex® Sinus-Max® Severe Congestion & Pain.